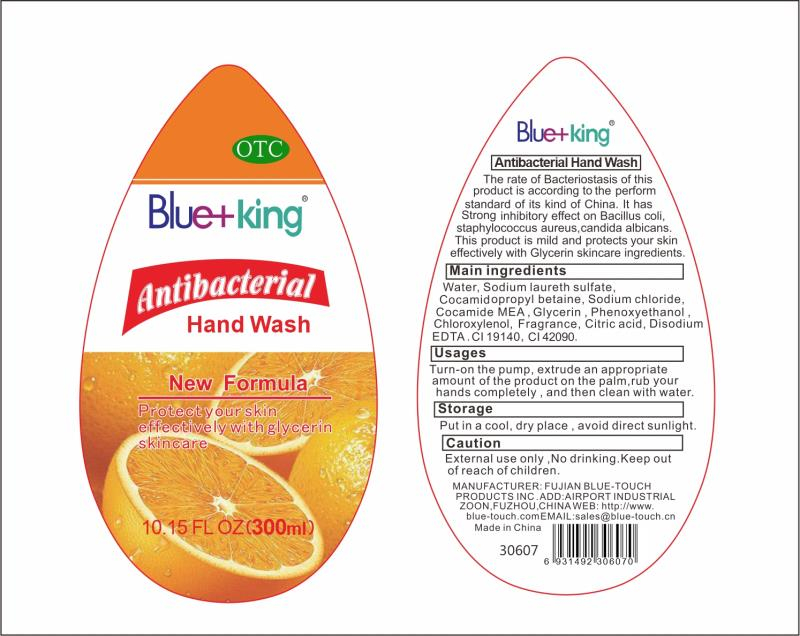 DRUG LABEL: Hand wash
NDC: 52578-001 | Form: LIQUID
Manufacturer: FUJIAN BLUE-TOUCH PRODUCTS INC.
Category: otc | Type: HUMAN OTC DRUG LABEL
Date: 20220220

ACTIVE INGREDIENTS: SODIUM LAURETH SULFATE 33 g/300 mL
INACTIVE INGREDIENTS: COCO MONOETHANOLAMIDE; WATER; COCAMIDOPROPYL BETAINE; SODIUM CHLORIDE; PHENOXYETHANOL; CHLOROXYLENOL; EDETATE DISODIUM ANHYDROUS; FRAGRANCE LAVENDER & CHIA F-153480; GLYCERIN; CITRIC ACID MONOHYDRATE

DOSAGE AND ADMINISTRATION

Put in a cool, dry place , avoid direct sunlight.

INACTIVE INGREDIENT

Water, ,Cocamid opropyI betaine, Sodium chloride,Cocamide MEA , Glycerin , Phenoxyethanol ,Chloroxylenol, Fragrance, Citric acid, Disodium EDTA

INDICATIONS AND USAGE

Turn-on the pump, extrude an appropriate amount of the product on the palm,rub your hands completely，and then clean with water.

ACTIVE INGREDIENT

SODIUM LAURETH SULFATE

keep out of reach of children

PURPOSE

Disinfection
Sterilization
No Rinseing

WARNINGS

External use only ,No drinking. Keep out of reach of children.